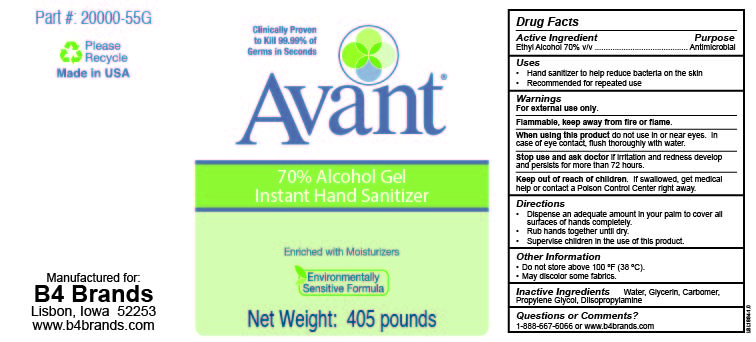 DRUG LABEL: Avant 70% Alcohol Gel
NDC: 68306-116 | Form: GEL
Manufacturer: B4 Ventures LLC
Category: otc | Type: HUMAN OTC DRUG LABEL
Date: 20231120

ACTIVE INGREDIENTS: ALCOHOL 70 mL/100 mL
INACTIVE INGREDIENTS: WATER; GLYCERIN; CARBOMER HOMOPOLYMER TYPE C (ALLYL PENTAERYTHRITOL CROSSLINKED); PROPYLENE GLYCOL; DIISOPROPYLAMINE

B4 Brands: Avant 70% Alcohol Gel - Instant Hand Sanitizer

Active Ingredient

Ethyl Alcohol 70% v/v

Purpose

Antimicrobial

Uses

- Hand sanitizer to help reduce bacteria on the skin
- Recommended for repeated use

Warnings

For external use only.

Flammable, keep away from fire or flame.

When using this product do not use in or near eyes. In case of eye contact, flush thoroughly with water.

Stop use and ask doctor if irritation and redness develop and persists for more than 72 hours.

Keep out of reach of children. If swallowed, get medical help or contact a Poison Control Center right away.

Directions

- Dispense an adequate amount in your palm to cover all surfaces of hands completely.
- Rub hands together until dry.
- Supervise children in the use of this product.

Other Information

- Do not store above 100 ºF (38 ºF).
- May discolor some fabrics.

Inactive Ingredients

Water, Glycerin, Carbomer, Propylene Glycol, Diisopropylamine

Questions or Comments?

1-888-667-6066 or www.b4brands.com